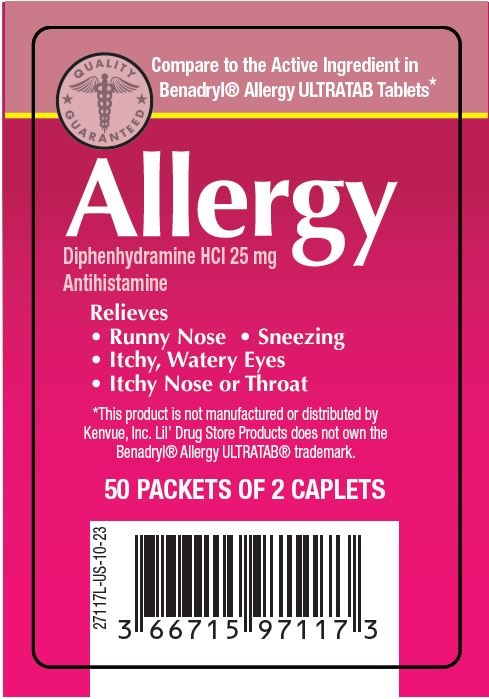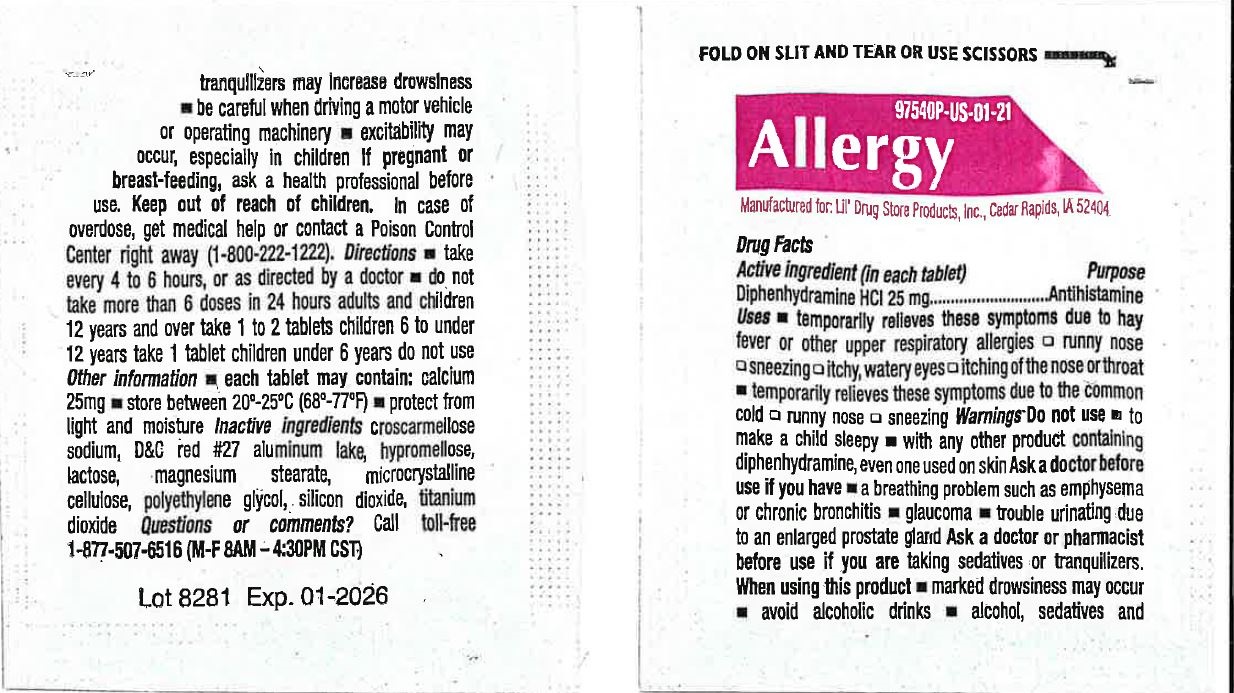 DRUG LABEL: Allergy
NDC: 66715-9711 | Form: TABLET
Manufacturer: Lil' Drug Store Products, Inc.
Category: otc | Type: HUMAN OTC DRUG LABEL
Date: 20231215

ACTIVE INGREDIENTS: DIPHENHYDRAMINE HYDROCHLORIDE 25 mg/1 1
INACTIVE INGREDIENTS: CROSCARMELLOSE SODIUM; D&C RED NO. 27; MAGNESIUM STEARATE; HYPROMELLOSE, UNSPECIFIED; LACTOSE, UNSPECIFIED FORM; CELLULOSE, MICROCRYSTALLINE; POLYETHYLENE GLYCOL, UNSPECIFIED; SILICON DIOXIDE; TITANIUM DIOXIDE

Allergy

Active Ingredient

Active ingredient (in each tablet)
Diphenhydramine HCl 25 mg

Purpose

Anrihistamine

Uses

- temporarily relieves these symptoms due to hay fever or other upper respiratory allergies
- runny nose
- sneezing
- itchy, watery eyes
- itching of the nose or throat
- temporarily relieves these symptoms due to the common cold
- runny nose
- sneezing

Warnings

Do not use

- to make a child sleepy
- with any other product containing diphenhydramine, even one used on skin

Ask a doctor before use if you have

- a breathing problem such as emphysema or chronic bronchitis
- glaucoma
- trouble urinating due to an enlarged prostate gland

Ask a doctor or pharmacist before use if you are

taking sedatives or tranquilizers.

When using this product

- marked drowsiness may occur
- avoid alcoholic drinks
- alcohol, sedatives and tranquilizers may increase drowsiness
- be careful when driving a motor vehicle or operating machinery
- excitability may occur, especially in children

PREGNANCY OR BREAST FEEDING

If pregnant or breast-feeding, ask a health professional before use.

Keep out of reach of children. In case of overdose, get medical help or contact a Poison Control Center right away (1-800-222-1222).

Directions

- take every 4 to 6 hours, or as directed by a doctor
- do not take more than 6 doses in 24 hours
- adults and children 12 years and over take 1 to 2 tablets
- children 6 to under 12 years take 1 tablet
- children under 6 years do not use

Other information

- each tablet may contain: calcium 25mg
- store at room temperature 68º-77ºF (20º-25ºC)
- protect from light and moisture

Inactive ingredients

croscarmellose sodium, D&C red #27 aluminum lake, hypromellose, lactose, magnesium stearate, microcrystalline cellulose, polyethylene glycol, silicon dioxide, titanium dioxide

Questions or comments?

call toll-free 1-877-507-6516 (M-F 8AM – 4:30PM CST)

Allergy (Lil' Drug Store) Pouch & Sleeve Label - PDP/Package

[caduceus]

Compare to the active ingredient in

Benadryl® Allergy ULTRATAB Tablets*

Allergy

Diphenhydramine HCl 25 mg

Antihistamine

Relieves

• Runny Nose • Sneezing

• Itchy, Watery Eyes

• Itchy Nose or Throat

*This product is not manufactured or distributed by

Kenvue, Inc. Lil' Drug Store Products does not own the

Benadryl Allergy ULTRATAB® trademark.

50 PACKETS OF 2 CAPLETS

[UPC]

3 66715 97117 3